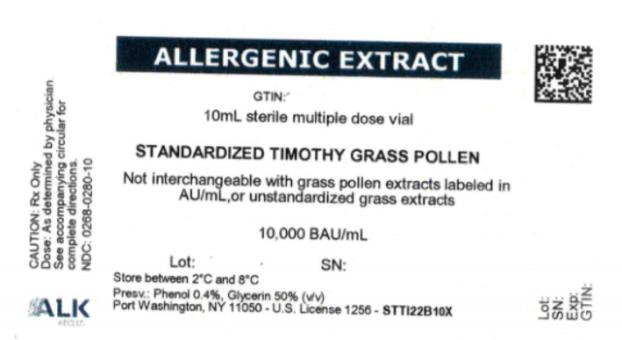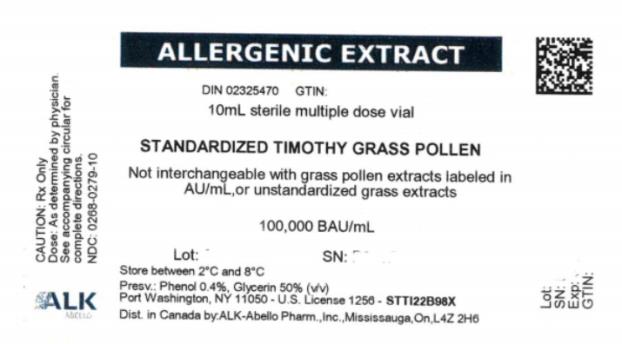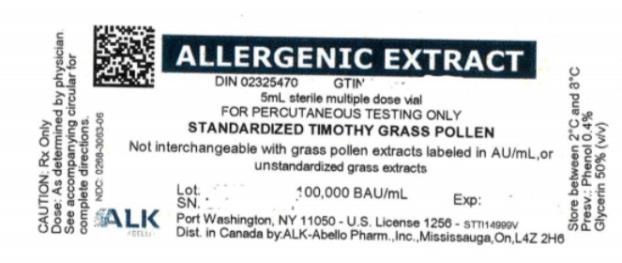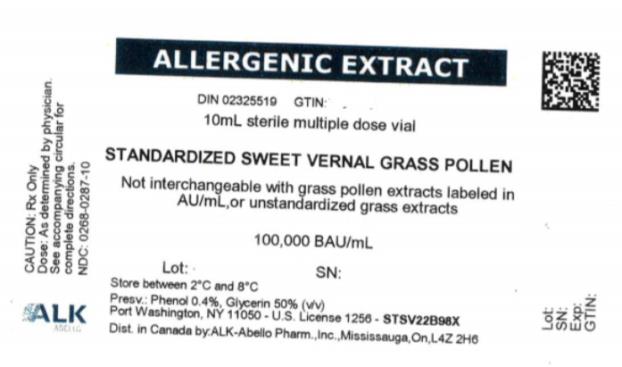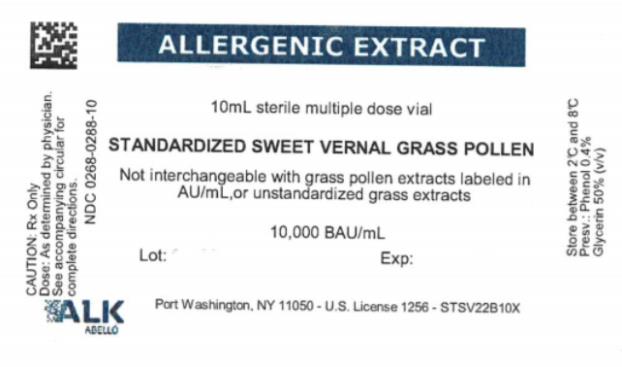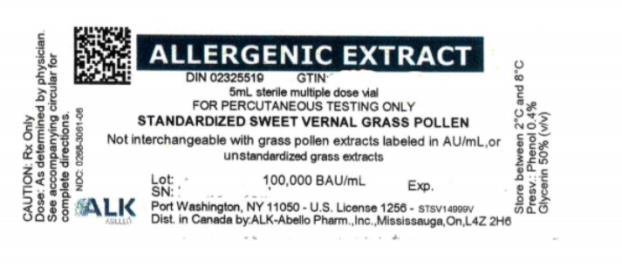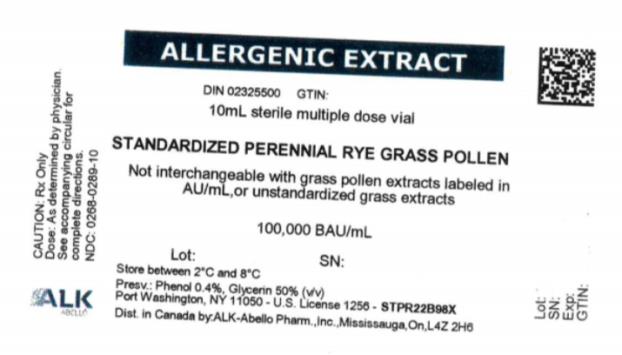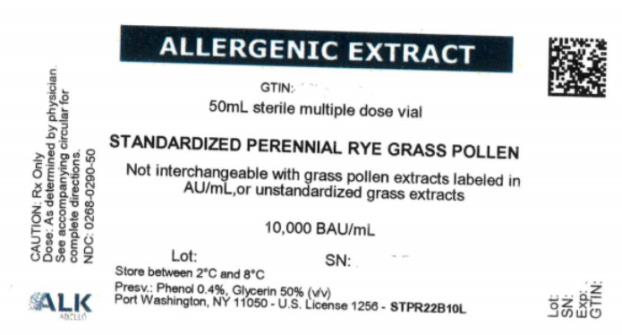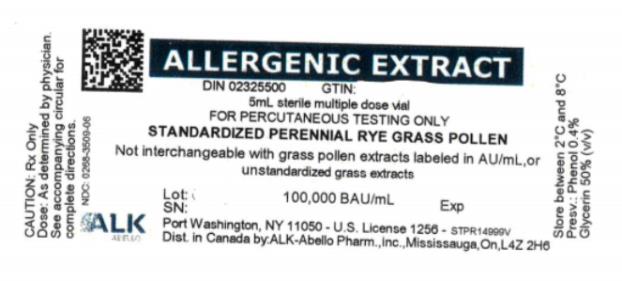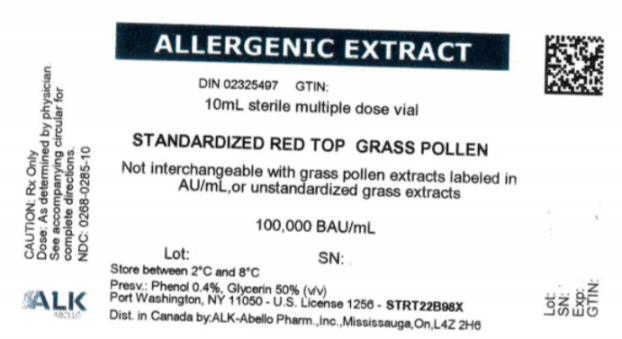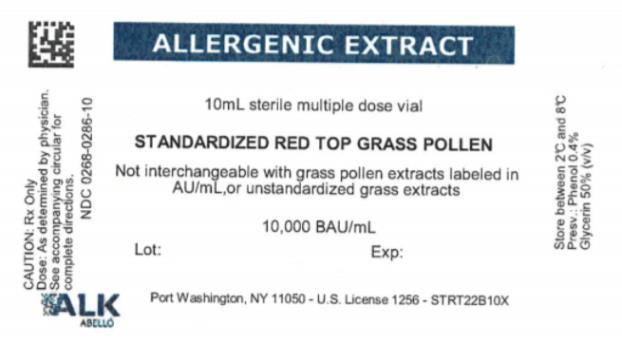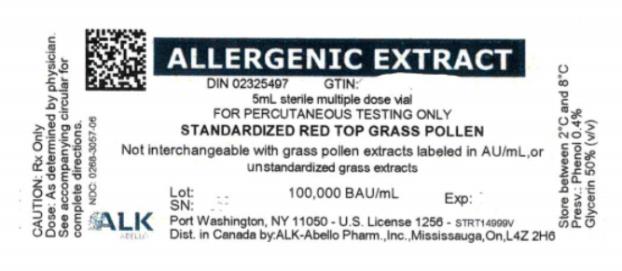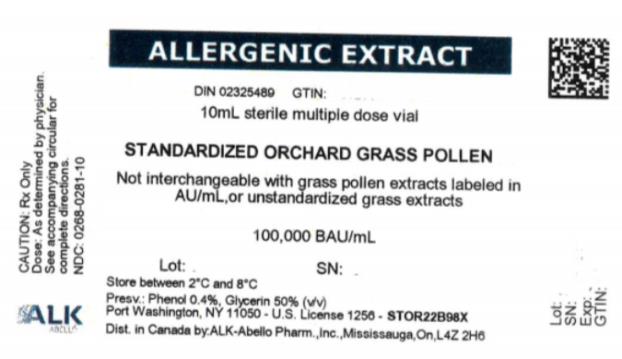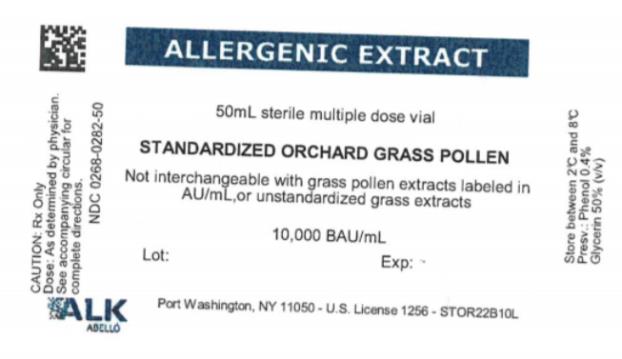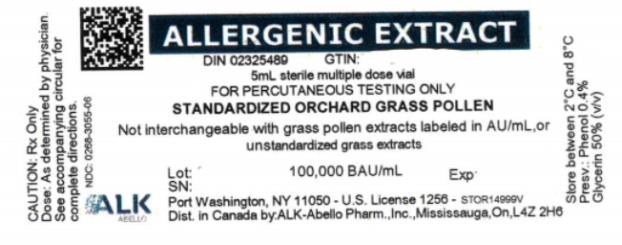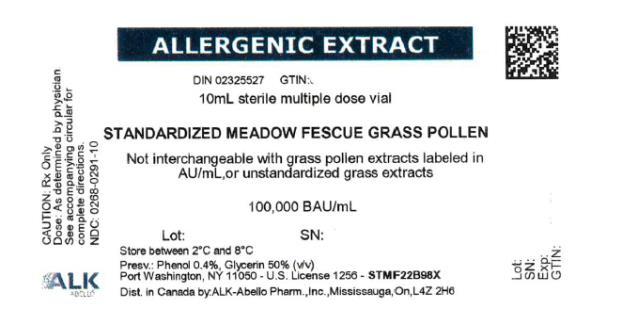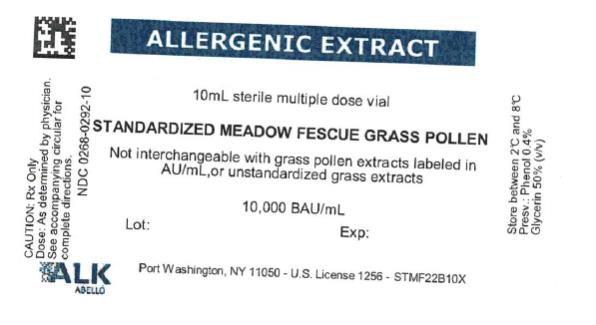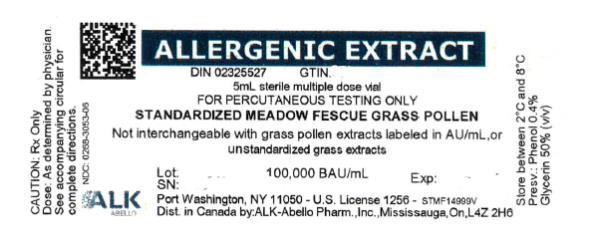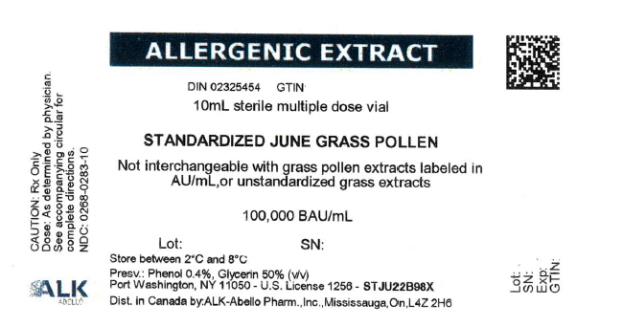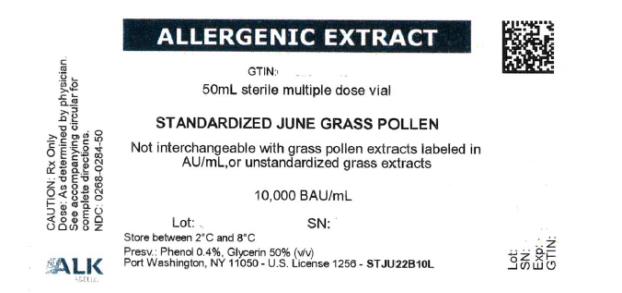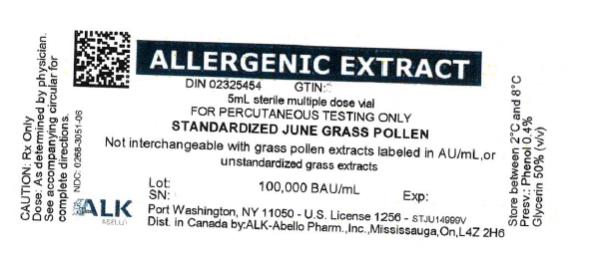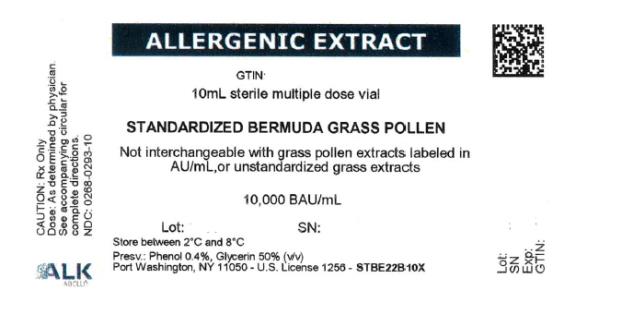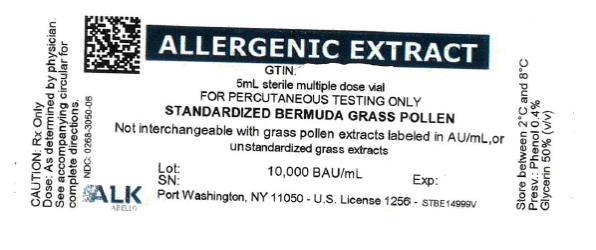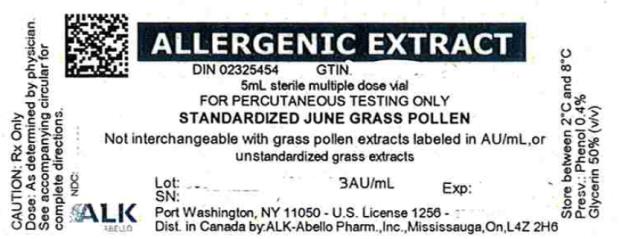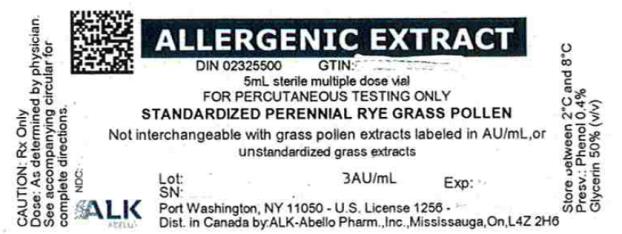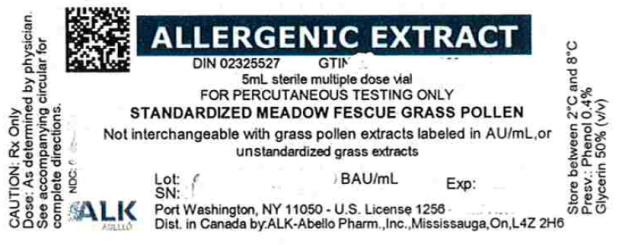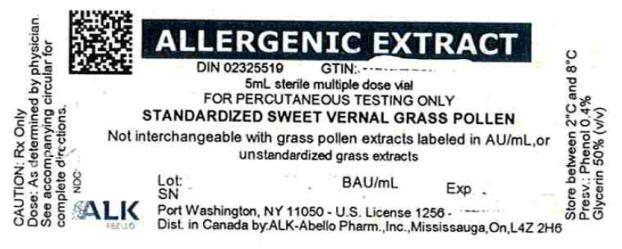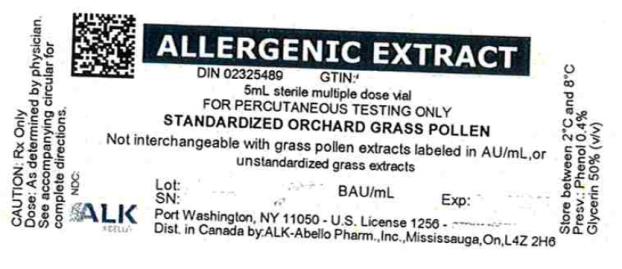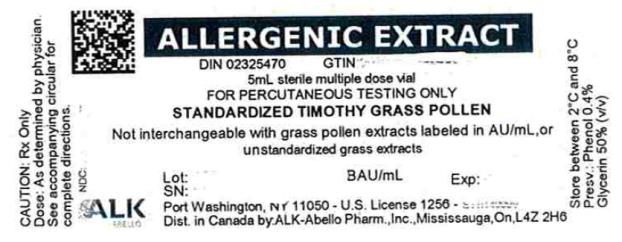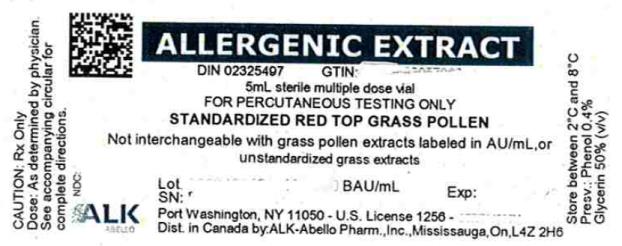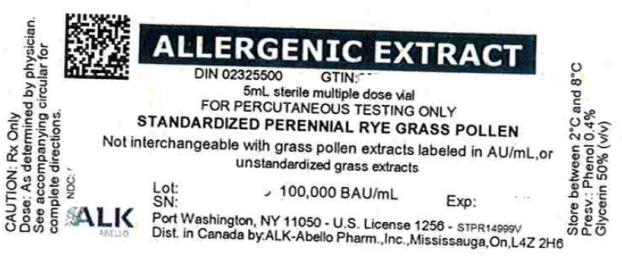 DRUG LABEL: Bermuda Grass, Standardized
NDC: 0268-3050 | Form: SOLUTION
Manufacturer: ALK-Abello, Inc.
Category: other | Type: STANDARDIZED ALLERGENIC
Date: 20230523

ACTIVE INGREDIENTS: CYNODON DACTYLON POLLEN 10000 [BAU]/1 mL
INACTIVE INGREDIENTS: SODIUM CHLORIDE 0.005 g/1 mL; SODIUM BICARBONATE 0.00275 g/1 mL; GLYCERIN 0.5 mL/1 mL; PHENOL 0.004 mL/1 mL; HYDROCHLORIC ACID; SODIUM HYDROXIDE

DIRECTIONS FOR USE OF ALLERGENIC EXTRACTS STANDARDIZED GRASS POLLENS

WARNING

Standardized allergenic extract is intended for use by physicians who are experienced in the administration of standardized (BAU/mL) allergenic extracts for immunotherapy and the emergency care of anaphylaxis, or for use under the guidance of an allergy specialist. Standardized allergenic extracts are not directly interchangeable with allergenic extracts of the same labeled potency from different manufacturers. The initial dose of standardized extract must be based on skin testing as described in the warnings, dosage and administration section of this insert.

Patients should be instructed to recognize adverse reaction symptoms and cautioned to contact the physician's office if reaction symptoms occur. As with all allergenic extracts, severe systemic reactions may occur. In certain individuals, these life-threatening reactions may be fatal.

Patients should be observed for at least 20 - 30 minutes following treatment, and emergency measures, as well as personnel trained in their use, should be immediately available in the event of a life-threatening reaction. Patients with unstable asthma or steroid dependent asthmatics and patients with underlying cardiovascular disease are at greater risk to a fatal outcome from a systemic allergic reaction.

This product should not be injected intravenously. It is intended for percutaneous and subcutaneous use. See the warnings, precautions, adverse reactions and overdosage sections below.

Patients receiving beta-blockers may not be responsive to epinephrine or inhaled bronchodilators. Respiratory obstruction not responding to parenteral or inhaled bronchodilators may require theophylline, oxygen, intubation and the use of life support systems. Parenteral fluid and/or plasma expanders may be utilized for treatment of shock. Adrenocorticosteroids may be administered parenterally or intravenously. Refer to the warnings, precautions and adverse reaction sections below.

Sensitive patients may experience severe anaphylactic reactions resulting in respiratory obstruction, shock, coma and/or death. Adverse events are to be reported to MedWatch (1-800-FDA-1088), Adverse Experience Reporting, HFM-210 Center for Biologics Evaluation & Research, Food & Drug Administration, 1401 Rockville Pike, Rockville, MD 20852-1448.

DESCRIPTION

Standardized allergenic extract of grass pollens from Timothy (Phleum pratense), Orchard (Dactylis glomerata), June (Poa pratensis), Red Top (Agrostis alba), Sweet Vernal (Anthoxanthum odoratum), Meadow Fescue (Festuca elatior), Perennial Rye (Lolium perenne), Bermuda Grass (Cynodon dactylon), in the accompanying vial are sterile, and contain glycerin 50% v/v and phenol 0.4% (preservative). Inert ingredients may include sodium chloride for isotonicity and sodium bicarbonate buffer.

Glycerinated pollen extracts, for subcutaneous injection for immunotherapy and/or percutaneous or intracutaneous testing (see Dosage and Administration section), are prepared from defatted dried pollen extracted in glycerinated Coca’s Fluid, filtered aseptically, and dispensed into multiple dose vials. These are subsequently tested for sterility, safety, and potency.

For ease in use and for lot-to-lot consistency, the potency is expressed in Bioequivalent Allergy Units (BAUs) per milliliter. A value of 10,000 BAU/mL is assigned to the CBER reference standard that can be diluted 1:0.5 million to produce intradermal ƩE (sum of Erythema) of 50 mm in highly puncture reactive subjects^1. A value of 100,000 BAU/mL is assigned to the CBER reference standard that can be diluted 1:5 million to produce intradermal ƩE (sum of Erythema) of 50 mm in highly puncture reactive subjects. The relative potency of each lot of standardized extract has been compared to the official CBER reference standard by an acceptable assay such as ELISA Inhibition.^2 When the potency is equivalent by ELISA Inhibition to the reference, the product is assigned 10,000 BAU/mL or 100,000 BAU/mL. Standardized grass pollen extracts, except for Bermuda, have potency designations of either 10,000 BAU/mL or 100,000 BAU/mL. Bermuda grass pollen extract is only available with a 10,000 BAU/mL potency designation.

In the ELISA Inhibition assay, a competitive binding assay, the wells of microtiter plates are coated using a characterized allergenic extract. Allergic sera is added to each well. The binding of IgE specific for the coating allergen is inhibited by concentrations of a test sample of an extract of the same allergen. The amount of IgE bound to the solid phase allergen (and subsequently the degree of inhibition) is determined using enzyme-labeled anti-human IgE antibodies and the appropriate substrate. The potency relative to a reference is determined using a parallel line bioassay method.

CLINICAL PHARMACOLOGY

Diagnostically (for skin testing) the allergen combines with IgE antibodies fixed to mast cells in the skin.^3 This complexing causes an increase in cellular permeability and degranulation of the mast cells releasing chemical mediators. These mediators (such as histamine) are responsible for a local inflammatory response of wheal and erythema typical of a positive skin test reaction and also, the symptoms commonly associated with allergic disease. The more mediator released, the larger the reaction (wheal and erythema).

Treatment consists of the subcutaneous injection of gradually increasing doses of the allergens to which the patient is allergic. It has been demonstrated that this method of treatment induces an increased tolerance to the allergens responsible for the symptoms on subsequent exposure. Although the exact relationships between allergen, skin-sensitizing antibody (IgE) and the blocking antibody (IgG) have not been precisely established, clinically confirmed immunological studies have adduced evidence of the efficacy of hyposensitization therapy.

Numerous controlled studies have demonstrated the clinical efficacy of immunotherapy with cat, dust mites and some pollen, including grass pollen extracts.^4 Nevertheless, responses are variable, and in a few studies patients reported no appreciable benefit.

Puncture test data with 10,000 BAU/mL Grass Pollen Extract CBER reference preparations, in 15 grass allergic patients yielded the following sizes of wheal and erythema (Ʃ = sum of longest diameter and orthogonal cross diameter). ^5

A. Puncture bifurcated needle data with 10,000 BAU/mL CBER Reference Grass Pollen Extract.

Reference | FDA |  | PƩErythema (mm) |  | PƩWheal (mm)
Pollen | Lot # | N | Mean | Range | Mean | Range
Bermuda | E4-Ber | 15 | 90.3 | 43-123 | 15.7 | 7-31
June | E3-Jkb | 15 | 77.3 | 47-107 | 15.9 | 6-28
Meadow Fescue | E4-MF | 15 | 81.1 | 57-115 | 11.9 | 7-22
Orchard | E4-Or | 15 | 84.3 | 57-111 | 14.1 | 9-19
Perennial Rye | E10-Rye | 15 | 92.3 | 73-135 | 17.5 | 6-36
Red Top | E4-Rt | 15 | 77.1 | 42-98 | 14.1 | 8-19
Sweet Vernal | E4-SV | 15 | 81.2 | 28-123 | 15.7 | 8-30
Timothy | E6-Ti | 15 | 88.3 | 51-109 | 16.9 | 8-40

The intradermal dose (BAU50) of the CBER (FDA) Grass Pollen Extract Reference Preparation required producing a 50 mm Sum of Erythema was calculated based on titration in sensitive individuals.

B. Intradermal Dose of CBER Reference Grass Pollen Extracts for 50mm Sum of Erythema Diameter (BAU50)^5.

Reference | FDA | BAU 50/mL
Pollen | Lot # | Mean | Range
Bermuda | E4-Ber | 0.02 | 0.4-0.0003
June | E3-Jkb | 0.02 | 0.1-0.004
Meadow Fescue | E4-MF | 0.02 | 0.9-0.002
Orchard | E4-Or | 0.02 | 1.9-0.002
Perennial Rye | E10-Rye | 0.02 | 0.7-0.002
Red Top | E4-Rt | 0.02 | 0.8-0.004
Sweet Vernal | E4-SV | 0.02 | 1.0-0.002
Timothy | E6-Ti | 0.02 | 0.6-0.002

INDICATIONS AND USAGE

Indicated use of allergenic extracts is for the diagnosis and treatment (hyposensitization therapy) of patients who experience allergic symptoms due to exposure to grass pollen and who exhibit type I skin sensitivity when tested to those specific allergens.

Hyposensitization (injection) therapy is a treatment for patients exhibiting allergic reactions to seasonal pollens, dust mites, molds, animal danders, and various other inhalants in situations where the offending allergen cannot be avoided.

For previously untreated patients, prior to the initiation of therapy, clinical sensitivity to the standardized grass pollen extract should be established by careful evaluation of the patient's history confirmed by diagnostic skin testing. Hyposensitization should not be prescribed for sensitivities to allergens which can easily be avoided.

10,000 BAU/mL extracts are indicated for percutaneous testing. If negative, the 100,000 BAU/mL dose may be used. Availability of 10,000 and 100,000 BAU/mL dosages facilitate safe switching. Patients who tolerate dilutions prepared from the 10,000 BAU/mL dosage and require a higher dose may be treated with dilutions prepared from the 100,000 BAU/mL dosage.

100,000 BAU/mL concentrations may be especially useful when patients are hyposensitized to numerous allergens. Mixing of allergenic extracts dilutes the potency of each constituent. Using higher concentrations such as 100,000 BAU/mL allows for dilution with other extracts without sacrificing immunizing properties. CAUTION: The final potency of each individual component in a patient mixture should never exceed 10,000 BAU/mL. See also, DOSAGE AND ADMINISTRATION section for discussion of mixture labeling.

CONTRAINDICATIONS

A patient should not be immunized with preparations of allergens to which the patient has not demonstrated symptoms, IgE antibodies, positive skin tests, or properly controlled challenge testing. In most cases, immunotherapy is not indicated for those allergens that can be eliminated or minimized by environmental control.

Patients on beta-blockers are not candidates for immunotherapy, as they can be non-responsive to beta-agonists that may be required to reverse a systemic reaction (also see WARNINGS and ADVERSE REACTIONS). In the presence of active symptoms such as rhinitis, wheezing, dyspnea, etc., the indications of immunotherapy must be weighed carefully against the risk of temporarily aggravating the symptoms by the injection itself.

Also, there is some evidence, although inconclusive, that routine immunizations may exacerbate autoimmune diseases. ^6,7,8 Hyposensitization should be given cautiously to patients with this predisposition. Patients with severe cardiorespiratory symptoms are at an additional risk during a systemic reaction. The physician must weigh risk to benefit in these cases.

WARNINGS

See warnings at the beginning of this package insert.

Patients should always be observed for at least 20 - 30 minutes after any injection. In the event of a marked systemic reaction (for a description of systemic reactions see Adverse Reaction Section), application of a tourniquet above the injection site and intramuscular administration of 0.2 mL to 1.0 mL (0.01 mg/kg) of Epinephrine Injection (1:1000) is recommended. This dose can be repeated after 15 minutes, as needed. Maximal recommended dose for children between 2 and 12 years of age is 0.5 mL. The tourniquet is then gradually released at 15 minute intervals. Patients under treatment with beta-blockers may be refractory to the usual dose of epinephrine. DO NOT GIVE ALLERGENIC EXTRACTS INTRAVENOUSLY.

Volume expanders and vasopressor agents may be required to reverse hypotension. Inhalation bronchodilators and parenteral aminophylline may be required to reverse bronchospasm. In cases of respiratory obstruction, oxygen and intubation may be necessary. Life-threatening reactions unresponsive to the above may require cardiopulmonary resuscitation.

A reduction in starting dose is recommended in the following circumstances:

1. Change to a new lot of extract from the same manufacturer;
2. Change to a different manufacturers extract;
3. Change in the extract formula;
4. Change to an extract bearing a later expiration date;
5. When a prolonged lapse in time has occurred since the last injection.

Withhold allergenic extracts temporarily or reduce the dose in patients with any one of the following conditions:

- Severe rhinitis or asthma symptoms;
- Infection or flu accompanied by fever;
- Exposure to excessive amounts of clinically relevant allergen prior to therapy.

Allergenic extracts slowly become less potent with age. During the course of treatment, it may be necessary to continue therapy with a vial of extract bearing a later expiration date. The initial dose of the extract bearing the later expiration date should be lowered to a safe non-reaction-eliciting level. When switching one standardized extract with another, at least 75% reduction in dose is suggested.

Patients with unstable asthma or steroid dependent asthmatics and patients with underlying cardiovascular disease are at greater risk to a fatal outcome from a systemic allergic reaction^12.

See also PRECAUTIONS and ADVERSE REACTIONS.

PRECAUTIONS

Information for Patients: Patients should be instructed to describe any active allergic symptoms such as rhinitis, wheezing, dyspnea, etc. prior to injection including any late reactions from previous administration. Patients should be instructed to remain in the office for 20 to 30 minutes after injection to monitor for adverse reactions. Also, see ADVERSE REACTIONS and WARNINGS sections.

General:

1. In the presence of active symptoms such as rhinitis, wheezing, dyspnea, etc., the indications of immunotherapy must be weighed carefully against the risk of temporarily aggravating the symptoms by the injection itself. Objective assessment of pulmonary function such as Peak Expiratory Flow Rate (PEFR) before allergen administration and prior to discharge may be useful in unstable asthmatics to reduce the chances of exacerbation of the patient’s asthma. If the protective action of allergenic extract injections is considered essential for the patient's welfare, appropriate symptomatic therapy with antihistaminic, beta-adrenergic or other drugs might be needed either prior to or in conjunction with the allergenic extract injections.
2. Store allergenic extracts between 2o and 8oC at all times, even during use.
3. Injections are to be given subcutaneously with the usual sterile precautions using a Tuberculin syringe.
4. Care must be taken to avoid injecting into a blood vessel. Pull gently on syringe plunger to determine if a blood vessel has been entered (See boxed Warnings).
5. Use standard aseptic precautions when making dilutions.
6. Extracts in 50% glycerin can cause discomfort at the site of the injection during the injection. Glycerinated extracts diluted for intradermal testing must be diluted at least twenty-five-fold to less than 2% glycerin (by volume), as glycerin above this level can cause false positive intradermal skin tests. Use of negative control skin test containing an equal concentration of glycerin as the allergen when evaluating intradermal skin tests is recommended.
7. Standardized concentrates of allergenic extracts must be diluted prior to initiation of immunotherapy.

Pregnancy - Category C:

Animal reproduction studies have not been conducted with allergenic extracts. It is also not known whether allergenic extracts can cause fetal harm when administered to a pregnant woman, or can affect reproduction capacity.

Controlled studies of hyposensitization with moderate to high doses of allergenic extracts during conception and all trimesters of pregnancy have failed to demonstrate any risk to the fetus or to the mother^13. However, on the basis of histamine's known ability to contract the uterine muscle, the release of significant amounts of histamine from allergen exposure of hyposensitization overdose should be avoided on theoretical grounds. Therefore, allergenic extracts should be used cautiously in a pregnant woman, and only if clearly needed.

Pediatric Use:

Children can receive the same dose as adults, however, to minimize discomfort associated with dose volume it may be advisable to reduce the volume of the dose by one-half and administer the injection at two different sites.

Geriatric Use: Studies in geriatric patients have not been conducted. Physicians should consider risk to benefit of immunotherapy in this patient population.

Nursing Mothers:

It is not known whether this drug is excreted in human milk. Because many drugs are excreted in human milk, caution should be exercised when allergenic extracts are administered to a nursing woman.

Carcinogenesis, Mutagenesis, Impairment of Fertility:

Studies in animals have not been performed.

Drug Interactions:

Drugs can interfere with the performance of skin tests.^9

Antihistamines: Response to mediator (histamine) released by allergens is suppressed by antihistamines. The length of suppression varies and is dependent on individual patient, type of antihistamine and length of time the patient has been on antihistamines. The duration of this suppression may be as little as 24 hours to several days.

Tricyclic Antidepressants: These exert a potent and sustained decrease of skin reactivity to histamine which may last for a few weeks.

Beta2 Agonists: Oral terbutaline and parenteral ephedrine, in general, have been shown to decrease allergen induced wheal.

Dopamine: Intravenous infusion of dopamine may inhibit skin test responses.

Beta Blocking Agents: Propranolol can significantly increase skin test reactivity (see boxed Warnings).

Other Drugs: Short acting steroids, inhaled beta2 agonists, theophylline and cromolyn do not seem to affect skin test response.

ADVERSE REACTIONS

Local:

Reactions at the site of injection may be immediate or delayed. Immediate wheal and erythema reactions are ordinarily of little consequence; but if very large, may be the first manifestation of a systemic reaction. If large local reactions occur, the patient should be observed for systemic symptoms for which treatment is outlined below. However, systemic reactions may occur in the absence of large local reactions.

Delayed reactions start several hours after injection with local edema, erythema, itching or pain. They are usually at their peak at 24 hours, and usually require no treatment. Antihistamine drugs may be administered orally.

The next therapeutic dose should be reduced to the dose which did not elicit a reaction, and subsequent doses increased more slowly, i.e., use of intermediate dilutions.

Systemic:

It should be noted that anaphylaxis and deaths following the injection of mite and other extracts, including grass pollen extracts have been reported by The British Committee on Safety in Medicine.^10 Fatalities from immunotherapy in the United States since 1945 have been extensively reviewed by Lockey, R. F., et al.^11 , Reid, M.J., et al.^12 and also more recently by Bernstein, D. I. et al.^15 . With careful attention to dosage and administration, such reactions occur infrequently, but it must be remembered that allergenic extracts are highly potent to sensitive individuals and OVERDOSE could result in anaphylactic symptoms. Therefore, it is imperative that physicians administering allergenic extracts understand and be prepared for the treatment of severe reactions.

Systemic reactions are characterized by one or more of the following symptoms: sneezing, mild to severe generalized urticaria, itching, other than at the injection site, extensive or generalized edema, wheezing, asthma, dyspnea, cyanosis, hypotension, syncope and upper airway obstruction. Symptoms may progress to shock and death. Patients should always be observed for at least 20 - 30 minutes after any injection. Volume expanders and vasopressor agents may be required to reverse hypotension. Inhalational bronchodilators and parenteral aminophylline may be required to reverse bronchospasm. Severe airway obstruction, unresponsive to bronchodilator, may require tracheal intubation and use of oxygen. In the event of a marked systemic reaction, application of a tourniquet above the injection site and the administration of 0.2 mL to 1.0 mL of Epinephrine Injection (1:1000) intramuscular is recommended. Maximal recommended dose for children under 2 years of age is 0.3 mL. Maximal recommended dose for children between 2 and 12 years of age is 0.5 mL. The tourniquet should not be left in place without loosening for 90 seconds every 15 minutes.

The next therapeutic injection of extract should be reduced to the dose which did not elicit a reaction, and subsequent doses increased more slowly; i.e., use of intermediate dilutions.

Adverse Events should be reported via MedWatch (1-800-FDA-1088), Adverse Experience Reporting, HFM-210 Center for Biologics Evaluation & Research, Food & Drug Administration, 1401 Rockville Pike, Rockville, MD 20852-1448.

OVERDOSAGE

Signs and symptoms of overdose are typically local and systemic reactions. For a description and management of overdose reactions, refer to "Adverse Reactions" section above.

DOSAGE AND ADMINISTRATION

Parenteral drug products should be inspected visually for particulate matter and discoloration prior to administration whenever solution and container permit.

When diluting bulk extracts, use of Sterile Diluent for Allergenic Extracts or Sterile Diluent for Allergenic Extracts Normal Saline with HSA are recommended. Dilutions should be made with sterile disposable syringes using aseptic technique. Commonly 10 fold dilutions are used to achieve a desired concentration for intradermal testing or initiation and continuation of immunotherapy. For example transferring 0.5 mL of a 10,000 BAU/mL extract into 4.5 mL of diluent will yield 5 mL of extract at 1,000 BAU/mL. Prepare as many additional serial dilutions as necessary to reach the appropriate concentration.

Stock mixtures of grass pollen extracts are compounded from individual grass pollen extracts. The total potency per milliliter (mL) of these mixtures is described on the container label, where space permits. The contribution each individual component is expressed in the supplemental labeling accompanying the vial.

Diagnosis –

In diagnosing the sensitive individual, the symptom history must be associated with exposure to the allergen. Skin testing is used in conjunction with a definitive history for diagnosing individual sensitivities.

An excellent method of recording results is to cover the skin reaction with transparent tape, outline the erythema first then the wheal with an indelible pen, then remove the tape and transfer it to the patient's permanent record. For preferred results, it is recommended that the actual measurement of the extent of both responses be recorded. This can be accomplished by measuring the longest erythema diameter, then selecting the mid-point of that line and measuring at a 90o angle to that line to determine the orthogonal diameter. The sum of these two measurements is the sum of erythema (ƩE); the sum of wheal diameters is determined in a similar manner.

Patient's response is graded on the basis of the size of erythema and/or wheal.

Percutaneous (prick/scratch/puncture) test:

Prick, scratch, or puncture skin tests should be performed initially using a glycerinated extract at 10,000 BAU/mL.

What follows are general guidelines for percutaneous testing^14. Different devices and/or techniques influence the size of the reaction, therefore it is important to refer to the device manufacturer's or distributor's instructions when grading reactions. As a negative control the diluent should be tested and included in the interpretation in the skin test reactions. Use of a positive control such as histamine base at 1 mg/mL should be used to assess skin test reactivity.

0 | No reaction or less than control
+ | Erythema greater than control, smaller than a nickel (21 mm diameter)
++ | Erythema greater than a nickel in diameter, no wheal
+++ | Wheal and erythema without pseudopods
++++ | Wheal and erythema with pseudopods

Intradermal test:

Intradermal testing should start with a dilute solution, usually in the range of 0.1 BAU/mL or less.

Glycerinated extracts diluted for intradermal testing may be diluted at least 25-fold to less than 2% glycerin (by volume) as glycerin above this level can cause false positive intradermal skin tests. Use a negative control skin test with glycerin content equal to the glycerin content of the allergen dose used for intradermal testing. Use of a positive control such as histamine base at 0.1 mg/mL or 0.01 mg/mL should be used to test reactivity.

On the forearm or upper outer aspect of the arm, using a 26 - 27 gauge, short bevel needle, inject intradermally 0.05 mL of the intradermal test solution. Skin whealing responses should be observed 10 - 20 minutes after administering the test.

A negative skin test is one where the sum of erythema was 0 or equal to the sum of the wheal. As a negative control, the diluent should be tested and included in the interpretation of the skin reactions. What follows are general guidelines intradermal testing ^14.

0 | No reaction or less than negative control
+ | 3-4 mm wheal with erythema, or erythema alone larger than a nickel (21 mm diameter)
++ | 4-8 mm wheal and erythema without pseudopods
+++ | Over 8 mm wheal and erythema without pseudopods
++++ | Wheal and erythema with pseudopods

Immunotherapy -

Starting dose for immunotherapy is related directly to a patient's sensitivity as determined by carefully executed skin testing. Degree of sensitivity can be established by determination of D50 (the intradermal dose, base three, that produces a ƩE = 50 mm).^1

A general rule is to begin at 1/10 of the dose that produces sum of erythema of 50 mm (approximately a 2+ positive skin test reaction). For example, if a patient exhibits a 2+ intradermal reaction to 1 BAU/mL, the first dose should be no higher than 0.05 mL of 0.1 BAU/mL. Dosage may be increased by 0.05 mL each time until 0.5 mL is reached, at which time the next 10-fold more concentrated dilution can be used, beginning with 0.05 mL, if no untoward reaction is observed.

If a tolerated dose of allergenic extract has been established, the initial dose from the new extract should be reduced to 25% of the previously well tolerated dose (see also Precautions).

Interval between doses in the early stages of immunotherapy is no more than once to twice a week, and may gradually be increased to once every two weeks. Generally, maintenance injections may be given as infrequently as once every two weeks to once a month.

Injections are given subcutaneously preferably in the arm. It is advantageous to give injections in alternate arms and routinely in the same area. In some patients, a local tolerance to the allergen may develop thus preventing a possible severe local reaction.

After inserting the needle, but before injecting the dose, pull plunger of the syringe slightly. If blood returns in the syringe, discard the syringe and contents and repeat injection at another site.

Bulk concentrated extracts must be diluted for initial therapy and intradermal skin testing. For recommended diluent, refer to DOSAGE AND ADMINISTRATION section.

Use standard aseptic precautions when making dilutions. The first dose of the new extract should be reduced at least 75% of the amount of the dosage from the previous extract.

Stability studies indicate that undiluted products will retain its potency under recommended storage conditions. Stability studies for undiluted forms of this product are not complete. It is recommended that minimal amounts of the concentrate be diluted so that the diluted product is used up within a relatively short period of time; i.e., preferably not more than four weeks.

HOW SUPPLIED

For percutaneous testing, 5 mL vial, 10,000 BAU/mL and 100,000 BAU/mL (except Bermuda grass 10,000 BAU/mL only) in glycerin 50% (v/v).

For immunotherapy, 10 mL, 30 mL, and 50 mL vials 10,000 BAU/mL in glycerin 50% (v/v), or 10 mL, 30 mL and 50 mL vials 100,000 BAU/mL in glycerin 50% (v/v). Bermuda is available only at 10,000 BAU/mL.

STORAGE:

To maintain stability of allergenic extracts, proper storage conditions are essential. Bulk concentrates and diluted extracts are to be stored at 2o to 8o C even during use. Bulk or diluted extracts are not to be frozen. Do not use after the expiration date shown on the vial label.

REFERENCES

^1Turkeltaub, P. C. et al. Office of Biologics Research and Review skin test method for evaluation of subject sensitivity to standardized allergenic extracts and for assignment of allergy units to reference preparations using the ID50EAL method. FDA CBER Methods of the Allergenic Products Testing Laboratory. 1993.

^2Miller, CA; Boyle, KT; and Braun, M. ELISA Competition Assay - Quantitative Determination of Relative Potency of Allergenic Extracts. FDA CBER Methods of the Allergenic Products Testing Laboratory. 1993.

^3Norman, P. S. The clinical significance of IgE. Hosp. Prac. 1975; 10:41-49.

^4Nelson, H.S. Immunotherapy for inhalant allergens. In: Middleton et al. Allergy Principles and Practice 6th Ed. St. Louis: CV Mosby, 2003;1455.

^5Data on file at FDA.

^6Umetsu, D. T. et al. Serum sickness triggered by anaphylaxis: a complication of immunotherapy. J. Allergy Clin. Immunol. 1985; 76:713.

^7Phannphak, P. and Kohler, P. F. Onset of polyarteritis nodosa during allergic hyposensitization treatment. Am. J. Med. 1980; 68:479.

^8Frank, M.M. and Hester, C.G. Immune complexes and allergic disease. In: Middleton et al.: Allergy Principles and Practice 6th Ed. St. Louis: CV Mosby, 2003:997.

^9Demoly, P., Piette, V., and Bousquet, J. In vivo methods for the study of allergy: skin test, techniques, and interpretation. In: Middleton et al.: Allergy Principles and Practice 6th Ed. St. Louis: CV Mosby, 2003:631.

^10Committee on the Safety of Medicines. CSM update: desensitizing vaccines. Brit. Med. J. 1986; 293:948.

^11Lockey, R. F. et al. Fatalities from immunotherapy(IT) and skin testing (ST). J. Allergy Clin. Immunol. 1987; 79:660.

^12Reid, M. J. et al. Survey of fatalities from skin testing and immunotherapy. 1985-1989. J. Allergy Clin Immunol. 1993; 92:6.

^13DuBuske L. M. et al. Special problems regarding Allergen Immunotherapy in Immunology and Allergy Clinics of North America, Greenburger, P.A. Ed. February 1992; 145-149.

^14Freedman, SO; Asthma and Allergic Rhinitis II Clinical Aspects. In Freedman and Gold Clinical Immunology, 2nd Ed. Hagerstown, MD: Harper & Row, 1976: 131.

^15Bernstein, D I, Wanner M. Borish L, Liss GM: Immunotherapy Committee, American Academy of Allergy, Asthma and Immunology. Twelve-year survey of fatal reactions to allergen injections and skin testing: 1990-2001. J. Allergy Clin Immunol. 2004 Jun; 113(6);1129-36.

Revision: November 2009

©ALK-Abello, Inc. 2009 187F

PRINCIPAL DISPLAY PANEL

ALLERGENIC EXTRACT
10mL sterile multiple dose vial
STANDARDIZED TIMOTHY GRASS POLLEN

PRINCIPAL DISPLAY PANEL

ALLERGENIC EXTRACT
5mL sterile multiple dose vial
FOR PERCUTANEOUS TESTING ONLY
STANDARDIZED TIMOTHY GRASS POLLEN

PRINCIPAL DISPLAY PANEL

ALLERGENIC EXTRACT
10mL sterile multiple dose vial
STANDARDIZED SWEET VERNAL GRASS POLLEN

PRINCIPAL DISPLAY PANEL

ALLERGENIC EXTRACT
5mL sterile multiple dose vial
FOR PERCUTANEOUS TESTING ONLY
STANDARDIZED SWEET VERNAL GRASS POLLEN

PRINCIPAL DISPLAY PANEL

ALLERGENIC EXTRACT
10mL sterile multiple dose vial
STANDARDIZED PERENNIAL RYE GRASS POLLEN

PRINCIPAL DISPLAY PANEL

ALLERGENIC EXTRACT
50mL sterile multiple dose vial
STANDARDIZED PERENNIAL RYE GRASS POLLEN

PRINCIPAL DISPLAY PANEL

ALLERGENIC EXTRACT
5mL sterile multiple dose vial
FOR PERCUTANEOUS TESTING ONLY
STANDARDIZED PERENNIAL RYE GRASS POLLEN

PRINCIPAL DISPLAY PANEL

ALLERGENIC EXTRACT
10mL sterile multiple dose vial
STANDARDIZED RED TOP GRASS POLLEN

PRINCIPAL DISPLAY PANEL

ALLERGENIC EXTRACT
5mL sterile multiple dose vial
FOR PERCUTANEOUS TESTING ONLY
STANDARDIZED RED TOP GRASS POLLEN

PRINCIPAL DISPLAY PANEL

ALLERGENIC EXTRACT
10mL sterile multiple dose vial
STANDARDIZED ORCHARD GRASS POLLEN

PRINCIPAL DISPLAY PANEL

ALLERGENIC EXTRACT
50mL sterile multiple dose vial
STANDARDIZED ORCHARD GRASS POLLEN

PRINCIPAL DISPLAY PANEL

ALLERGENIC EXTRACT
5mL sterile multiple dose vial
FOR PERCUTANEOUS TESTING ONLY
STANDARDIZED ORCHARD GRASS POLLEN

PRINCIPAL DISPLAY PANEL

ALLERGENIC EXTRACT
10mL sterile multiple dose vial
STANDARDIZED MEADOW FESCUE GRASS POLLEN

PRINCIPAL DISPLAY PANEL

ALLERGENIC EXTRACT
5mL sterile multiple dose vial
FOR PERCUTANEOUS TESTING ONLY
STANDARDIZED MEADOW FESCUE GRASS POLLEN

PRINCIPAL DISPLAY PANEL

ALLERGENIC EXTRACT
10mL sterile multiple dose vial
STANDARDIZED JUNE GRASS POLLEN

PRINCIPAL DISPLAY PANEL

ALLERGENIC EXTRACT
50mL sterile multiple dose vial
STANDARDIZED JUNE GRASS POLLEN

PRINCIPAL DISPLAY PANEL

ALLERGENIC EXTRACT
5mL sterile multiple dose vial
FOR PERCUTANEOUS TESTING ONLY
STANDARDIZED JUNE GRASS POLLEN

PRINCIPAL DISPLAY PANEL

ALLERGENIC EXTRACT
10mL sterile multiple dose vial
STANDARDIZED BERMUDA GRASS POLLEN

PRINCIPAL DISPLAY PANEL

ALLERGENIC EXTRACT
5mL sterile multiple dose vial
FOR PERCUTANEOUS TESTING ONLY
STANDARDIZED BERMUDA GRASS POLLEN